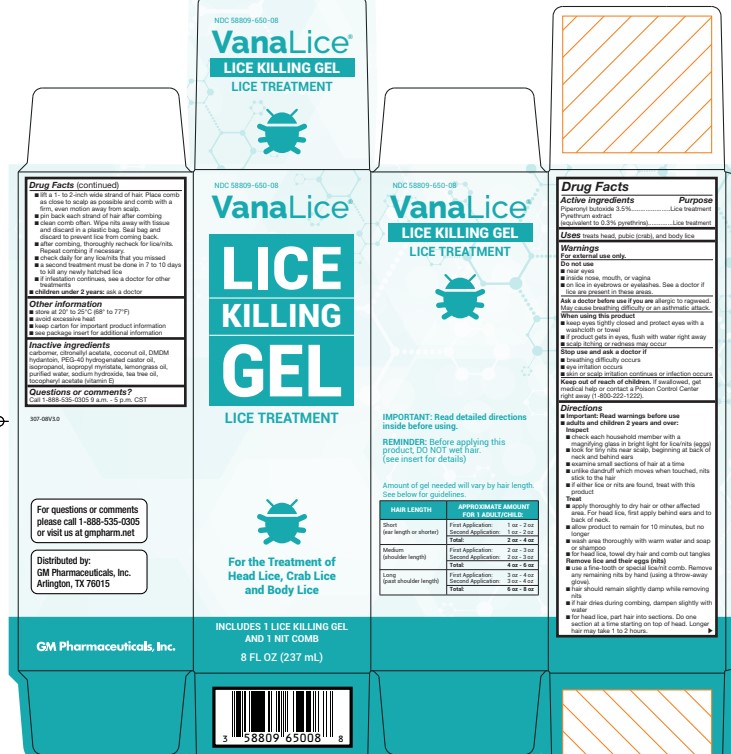 DRUG LABEL: Vanalice
NDC: 58809-650 | Form: GEL
Manufacturer: GM Pharmaceuticals, INC
Category: otc | Type: HUMAN OTC DRUG LABEL
Date: 20251203

ACTIVE INGREDIENTS: PIPERONYL BUTOXIDE 35 mg/1 mL; PYRETHRUM EXTRACT 3 mg/1 mL
INACTIVE INGREDIENTS: CARBOMER INTERPOLYMER TYPE A (55000 CPS); CITRONELLYL ACETATE; COCONUT OIL; DMDM HYDANTOIN; POLYOXYL 40 HYDROGENATED CASTOR OIL; ISOPROPYL MYRISTATE; WEST INDIAN LEMONGRASS OIL; WATER; SODIUM HYDROXIDE; TEA TREE OIL

Vanalice

VanaLice Lice Killing Gel Lice Treatment - piperonyl butoxide, pyrethrum extract

8 FL OZ.

VanaLice Lice Killing Gel Lice Treatment Drug Facts

ACTIVE INGREDIENT

Piperonyl butoxide 3.5%

Pyrethrum extract (equivalent to 0.3% pyrethrins)

PURPOSE

Lice treatment

Uses

treats head, pubic (crab), and body lice

WARNINGS

For external useonly

DO NOT USE

- near eyes
- inside nose, mouth, or vagina
- on lice in eyebrows or eyelashes. See a doctor if lice are present in these areas.
- if you have ever had an allergic reaction to this product or any of its ingredients

ASK DOCTOR

- allergic to ragweed. May cause breathing difficulty or an asthmatic attack.

WHEN USING

- keep eyes tightly closed and protect eyes with a washcloth or towel
- if product gets into eyes, flush with water right away
- scalp itching or redness may occur

STOP USE

- breathing difficulty occurs
- eye irritation occurs
- skin or scalp irritation continues or infection occurs

KEEP OUT OF REACH OF CHILDREN

If swallowed, get medical help or contact a Poison Control Center right away.

Directions

- Important: Read warnings before use Adults and children 2 years and over:

Inspect

- check each household member with a magnifying glass in bright light for lice/nits (eggs)
- look for tiny nits near scalp, beginning at back of neck and behind ears
- examine small sections of hair at a time
- unlike dandruff which moves when touched, nits stick to the hair
- if either lice or nits are found, treat with this product

Treat

- apply thoroughly to DRY HAIR or other affected area. For head lice, first apply behind ears and to back of neck.
- allow product to remain for 10 minutes, but no longer
- wash area thoroughly with warm water and soap or shampoo
- for head lice, towel dry hair and comb out tangles

Remove lice and their eggs (nits)

- use a fine-tooth or special lice/nit comb. Remove any remaining nits by hand (using a throw-away glove).
- hair should remain slightly damp while removing nits
- if hair dries during combing, dampen slightly with water
- for head lice, part hair into sections. Do one section at a time starting on top of the head. Longer hair may take 1 to 2 hours.
- lift a 1-to 2-inch wide strand of hair. Place comb as close to scalp as possible and comb with a firm, even motion away from scalp.
- pin back each strand of hair after combing
- clean comb often. Wipe nits away with tissue and discard in a plastic bag. Seal bag and discard to prevent lice from coming back.
- after combing, thoroughly recheck for lice/nits. Repeat combing if necessary.
- check daily for any lice/nits that you missed
- a second treatment must be done in 7 to 10 days to kill any newly hatched lice
- if infestation continues, see a doctor for other treatments

Children under 2 years: ask a doctor

Other information

- store at 20°-25°C (68°-77°F)
- avoid excessive heat
- keep carton for important product information
- see Consumer Information Insert for additional information

INACTIVE INGREDIENT

carbomer, citronellyl acetate, coconut oil, DMDM hydantoin, peg40-hydrogenated castor oil, isopropanol, isopropyl myristate, lemongrass oil, purified water, sodium hydroxide, tea tree oil tocopheryl acetate (vitamin E)

QUESTIONS

1-888-535-0305 Monday-Friday 9 AM - 5 PM CST

Step 1: Treat

VanaLice™ Lice Killing Gel

See Usage Guidelines to see how much product you will need.

NOTE:

- Use towels to protect child's eyes from treatment and prevent clothes from getting wet.
- Apply Lice Killing Gel thoroughly to DRY HAIR or other affected area.
- Wetting the hair dilutes the treatment making it less effective.
- Also, lice can hold their breath when immersed in water making it difficult for the active ingredient to penetrate the lice.
- For head lice, thoroughly massage Gel into scalp, behind the ears and to the back of the neck. Lice can crawl up and down the shaft of the hair very quickly so it is important to apply the treatment from the roots to the ends of the hair
- Allow product to remain on the hair (or other affected area) for 10 minutes, but no longer.
- Wash area thoroughly with warm water and soap or shampoo
- For head lice, towel dry hair and comb out tangles
- proceed to step 2
- A second treatment must be done in 7 to 10 days to kill any newly-hatched lice.

Step 2: Remove

Lice/Nit Comb

Combing must be done AFTER use of VanaLice™ Lice Killing Gel (Step 1). Combing out eggs & nits* is an

essential step to complete lice elimination.

NOTE:

- A fine-toothed comb or the special lice/nit removing comb (included) must be used to remove lice, eggs, and nits from hair.
- Before starting have on hand

- extra towels

- bobby pins or hair clips

- facial tissues or paper towels

- regular comb for parting and detangling hair

- detangler/conditioner to make combing easier

- Find a distraction for your child (e.g. books, TV, game).
- When combing, use the fine-tooth lice/nit comb provided and make sure the teeth are facing you
- Part hair into sections. Working one section at a time, lift a 1- to 2- inch wide strand of hair
- Place comb as a close to the scalp as possible and comb with a firm, even motion away from scalp, from the roots to the end of the hair (newly-laid eggs are found near the roots of the hair so it is important to get the teeth very close to the scalp). Make sure the teeth are deeply embedded into the strands as you comb through.
- Always comb away from the head.
- Wipe eggs and nits from the teeth of the comb with a tissue or paper towel.
- Remove any remaining nits by hand (using a throw-away-glove).
- Pin back the 1- to 2-inch wide strand you just finished combing with a bobby pin or hair clip.
- Lift up another 1- to 2-inch wide strand and repeat the combing procedure.
- When one section has been combed and pinned, repeat the process for another section of hair. Continue to comb hair 1- to 2-inches at a time until entire head has been combed and pinned.
- Keep the hair damp during combing and re-apply detangler/conditioner as needed.
- After you have combed and pinned the entire head, remove all bobby pins or hair clips and rinse hair thoroughly with warm water. If desired, you may also wash with regular shampoo.
- Discard all the used tissues or paper towels into a bag, seal and dispose to prevent lice from coming back.

*Nits are empty eggshells left behind when lice hatch from eggs.

Step 3 – Control

Head Lice

- Lay small white eggs (nits) on hair shaft close to scalp.
- Nits are most easily found on back of neck or behind ears.
- Disinfect hats, hair ribbons, scarves, coats, towels, and bed linens by machine washing in hot water [above 54°C (130°F)], then using hottest dryer cycle for at least 20 minutes.
- Items that cannot be washed (bedspreads, blankets, pillows, stuffed toys, etc.) should be dry- cleaned or sealed in a plastic bag for 4 weeks, then removed outdoors and shaken out very hard before using again.
- Items that cannot be washed, dry-cleaned, or stored may be sprayed with a product designed for this purpose.
- Soak all combs and brushes in hot water [above 54°C (130°F)] for at least 10 minutes.
- Vacuum all carpets, mattresses, upholstered furniture, and car seats that may have been used by affected people.

Pubic (Crab) Lice

- May be transmitted by sexual contact. Sexual partners should be treated simultaneously to avoid reinfestation.
- Lice are very small and look like brown or grey dots on skin.
- Usually cause intense itching and lay small white eggs (nits) on the hair shaft generally close to the skin surface.
- May be present on the short hairs of groin, thighs, trunk, and underarms, and occasionally on the beard and mustache.
- Disinfect underwear by machine washing in hot water [above 54°C (130°F)], then using hottest dryer cycle for at least 20 minutes.

Body Lice

- Body Lice and their eggs (nits) are generally found in the seams of clothing particularly in waistline and armpit area.
- Body Lice feed on skin then return to clothing to lay their eggs.
- Disinfect clothing by machine washing in hot water [above 54°C (130°F)], then using hottest dryer cycle for at least 20 minutes.
- Do not seal clothing in a plastic bag because nits can remain dormant for up to 30 days.

Daily Checking

TO PREVENT REINFESTATION:

- Carefully inspect infested family member daily for at least 2 weeks. If you see eggs or nits, repeat Step 2.
- Check other family members for Head Lice. If anyone in the family is infested, follow Step 1 and Step 2. Repeat Step 3 with any articles or items with which they have come into contact.

Checklist

- Home and auto upholstery

- Bike/sport helmets

- Mattresses, pillows, pillowcases

- Coats, scarves, earmuffs, gloves

- Bed linen

- Play mats

- Towels

- Clothing

- Stuffed animals, toys

- Barrettes/hair ornaments

- Headphones

- Hair rollers

- Hats

- Combs and brushes

- Headbands

- Baseball caps

PACKAGE LABEL

NDC 58809-650-08
VanaLice™
Lice
Killing
Gel
Lice Treatment
ONE NIT COMB INCLUDED

8 FL OZ (237 mL)